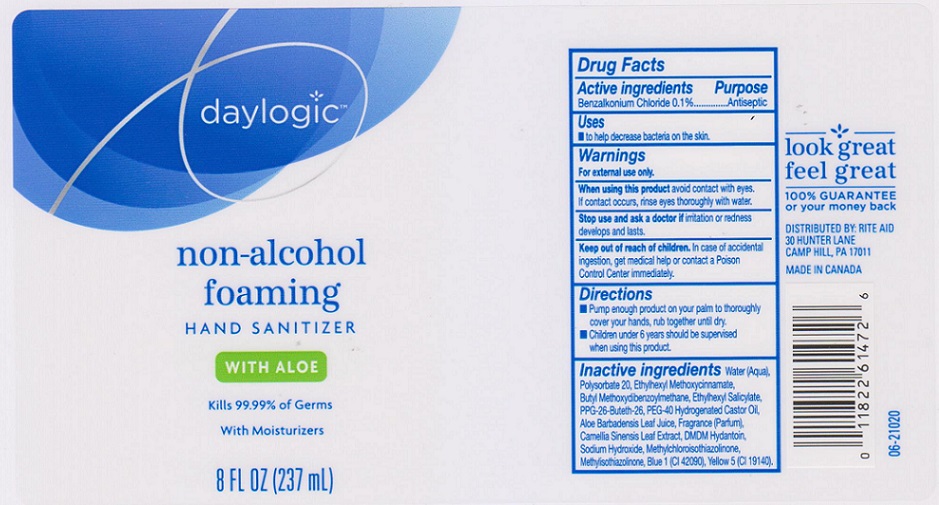 DRUG LABEL: Daylogic Foaming Sanitizer Aloe
NDC: 11822-2440 | Form: LIQUID
Manufacturer: RITE AID CORPORATION
Category: otc | Type: HUMAN OTC DRUG LABEL
Date: 20200323

ACTIVE INGREDIENTS: BENZALKONIUM CHLORIDE 1 mg/1 mL
INACTIVE INGREDIENTS: WATER; POLYSORBATE 20; OCTINOXATE; AVOBENZONE; OCTISALATE; PPG-26-BUTETH-26; POLYOXYL 40 HYDROGENATED CASTOR OIL; ALOE VERA LEAF; GREEN TEA LEAF; DMDM HYDANTOIN; SODIUM HYDROXIDE; METHYLCHLOROISOTHIAZOLINONE; METHYLISOTHIAZOLINONE; FD&C BLUE NO. 1; FD&C YELLOW NO. 5

DRUG FACTS

Active ingredient

Benzalkonium Chloride 0.1%

Purpose

Antiseptic

Uses

to help decrease bacteria on the skin.

Warnings

For external use only

When using this product

avoid contact with eyes. If contact occurs, rinse eyes thoroughly with water.

Stop use and ask a doctor if

irritation or redness develops and lasts.

Keep out of reach of children.

In case of accidental ingestion, get medical help or contact a Poison Control Center immediately.

Directions

- Pump enough product on your palm to thoroughly cover your hands, rub together until dry.
- Children under 6 years should be supervised when using this product.

Inactive ingredients

Water (Aqua), Polysorbate 20, Ethylhexyl Methoxycinnamate, Buty Methoxydibenzoylmethane, Ethylhexyl Salicyalte, PPG-26-Buteth-26, PEG-40 Hydrogenated Castor Oil, Aloe Barbadensis Leaf Juice, Fragrance (Parfum), Camellia Sinensis Leaf Extract, DMDM Hydantoin, Sodium Hydroxide, Methylchloroisothiazolinone, Methylisothiazolinone, Blue 1 (CI 42090), Yellow 5 (CI 19140).